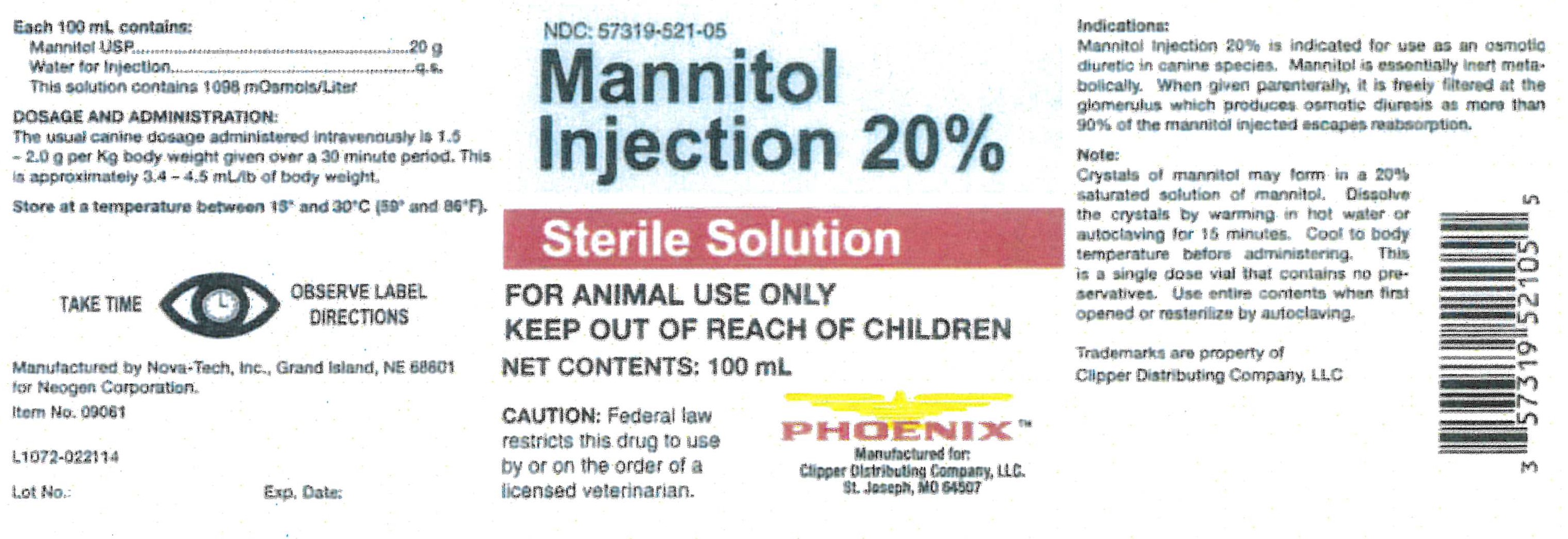 DRUG LABEL: Mannitol 20%
NDC: 57319-521 | Form: INJECTION
Manufacturer: Clipper
Category: animal | Type: PRESCRIPTION ANIMAL DRUG LABEL
Date: 20191122

ACTIVE INGREDIENTS: MANNITOL 20 g/100 mL
INACTIVE INGREDIENTS: WATER

Phoenix
MANNITOL Injection 20%

INDICATIONS:

Mannitol Injection 20% is indicated for use as an osmotic diuretic in canine species. Mannitol is essentially inert metabolically. When given parenterally, it is freely filtered at the glomerulus which produces osmotic diuresis as more than 90% of the mannitol injected escapes reabsorption.

Each 100 mL Contains:

Mannitol USP...................................20 g

Water for Injection...........................q.s.

This solution contains 1098 mOsmols/Liter

Dosage and Administration:

The usual canine dosage administered intravenously is 1.5 - 2.0 g per Kg body weight given over a 30 minute period. This is approximately 3.4-4.5 mL/lb of body weight.

Note:

Crystals of mannitol may form in a 20% saturated solution of mannitol. Dissolve the crystals by warming in hot water or autoclaving for 15 minutes. Cool to body temperature before administering. This is a single dose vial that contains no preservatives. Use entire contents when first opened or resterilize by autoclaving.

STORAGE AND HANDLING

Store at temperatures between 15°and 30°C (59°-86°F).

Manufactured by: Nova-Tech, Inc. Grand Island, NE 68801 for Neogen Corporation

Item No. 09061

1072-022114

Lot No.:

Exp. Date

NDC: 57319-521-05

Mannitol Injection 20%

Sterile Solution

Net Contentes: 100 mL

PhoenixTM

Manufactured for:

Clipper Distributing Company, LLC.

St. Joseph, MO 64507

Trademares are property of Clipper Distributing Company, LLC

WARNINGS AND PRECAUTIONS

Caution: Federal law restricts this drug to use by or on the order of a licensed veterinarian.

Take Time Observe Label Directions

FOR ANIMAL USE ONLY

KEEP OUT OF REACH OF CHILDREN